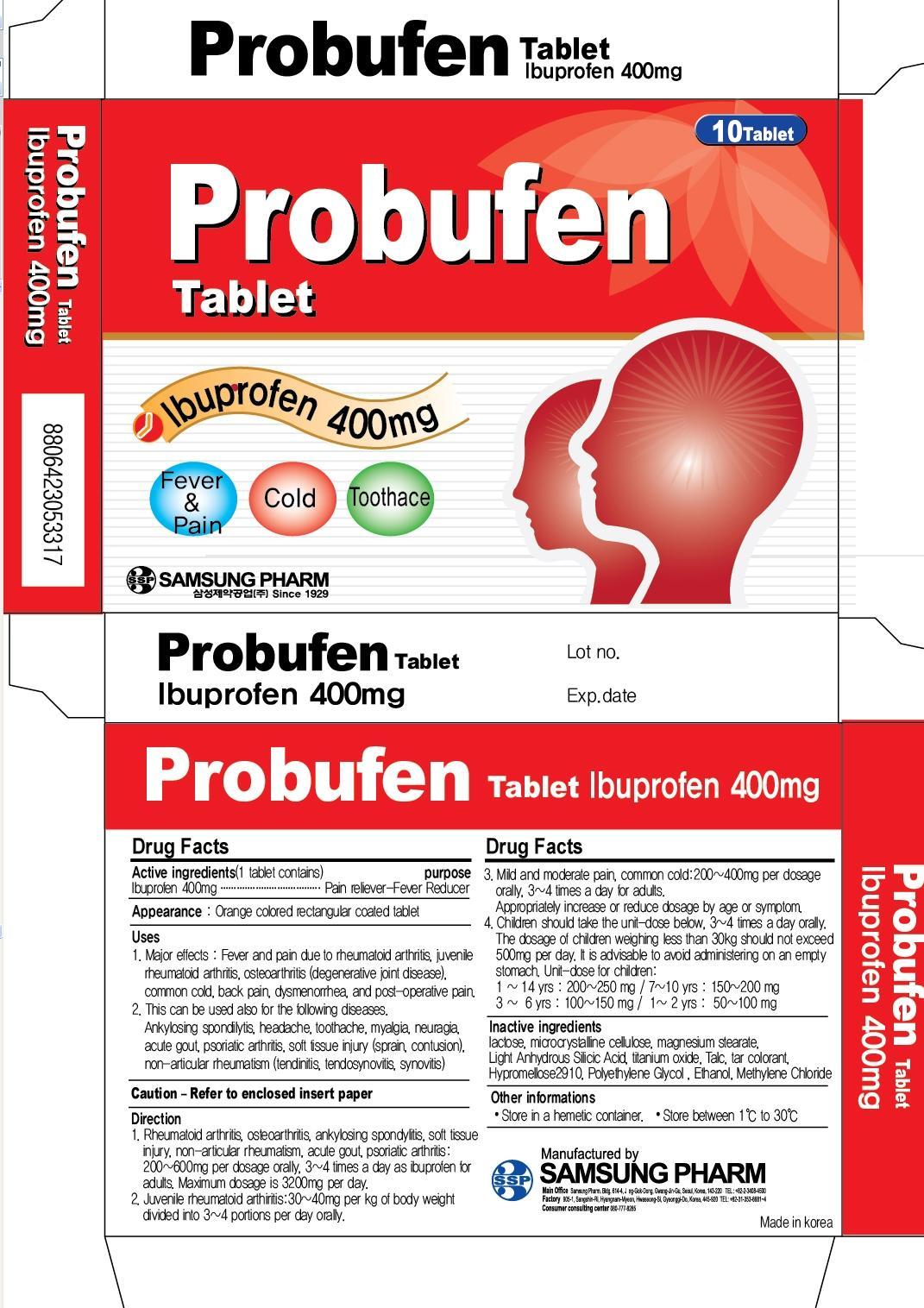 DRUG LABEL: PROBUFEN
NDC: 49789-050 | Form: TABLET
Manufacturer: SAMSUNG PHARM IND. CO., LTD.
Category: otc | Type: HUMAN OTC DRUG LABEL
Date: 20120904

ACTIVE INGREDIENTS: IBUPROFEN 400 mg/537 mg
INACTIVE INGREDIENTS: lactose; magnesium stearate; Talc; Methylene Chloride

ACTIVE INGREDIENT

ACTIVE INGREDIENT: Ibuprophen 400mg

INACTIVE INGREDIENT

Inactive ingredients:
lactose, microcrystalline cellulose, magnesium stearate, Light Anhydrous Silicic Acid, titanium oxide, Talc, tar colorant, Hypromellose2910, Polyethylene Glycol, Ethanol, Methylene Chloride

PURPOSE

PURPOSE: Pain reliever, Fever Reducer

DOSAGE AND ADMINISTRATION

Direction
1. Rheumatoid arthritis, osteoarthritis, ankylosing spondylitis, soft tissue injury, non-articular rheumatism, acute gout, psoriatic arthritis:
200-600mg per dosage orally, 3~4 times a day as ibuprofen for adults.
Maximum dosage is 3200mg per day.
2. Juvenile rheumatoid arthiritis:
30-40mg per kg of body weight divided into 3~4 portions per day orally.
3. Mild and moderate pain, common cold:
200-400mg per dosage orally, 3~4 times a day for adults.
Appropriately increase or reduce dosage by age or symptom.
4. Children should take the unit-dose below, 3~4 times a day orally.
The dosage of children weighing less than 30kg should not exceed 500mg per day.
It is advisable to avoid administering on an empty stomach.
Unit-dose for children:
11 - 14 yrs : 200 - 250 mg
7 - 10 yrs : 150 - 200 mg
3 - 6 yrs : 100 - 150 mg
1 - 2 yrs : 50 - 100 mg

INDICATIONS AND USAGE

Uses
1. Major effects
Fever and pain due to rheumatoid arthritis, juvenile rheumatoid arthritis, osteoarthritis (degenerative joint disease), common cold, back pain, dysmenorrhea, and post-operative pain.
2. This can be used also for the following diseases.
Ankylosing spondilytis, headache, toothache, myalgia, neuragia, acute gout, psoriatic arthritis, soft tissue injury (sprain, contusion), non-articular rheumatism (tendinitis, tendosynovitis, synovitis)

WARNINGS

WARNING
1. When those who drink alcohol over three glasses every day regularly with to take this drug or other antipyretic and analgesic, they must consult a doctor or pharmacist. Gastrointestinal bleeding may occur when these people take this drug.
2. Cardiovascular risks: Administering non-steroidal anti-inflammatory drugs (NSAIDs) including this product may lead to severe cardiovascular thrombotic response, myocardial infaction, and stroke. The possibility of abnormal cardiovascular reaction increases in patients with a period. Adverse reactions should be carefully monitored while an adverse reaction occurs.
3. Gastrointestinal risk: Administering NSAIDs including this product may cause severe gastrointestinal adverse reactions that may develop without any warning signs during the administration period. The risk of these adverse reactions increases in old age (elderly people) or in patients who have taken this drug for a long period.

KEEP OUT OF REACH OF CHILDREN

STORAGE AND HANDLING SECTION

Other informations:
Store in a hemetic container.
Store between 1C to 30C